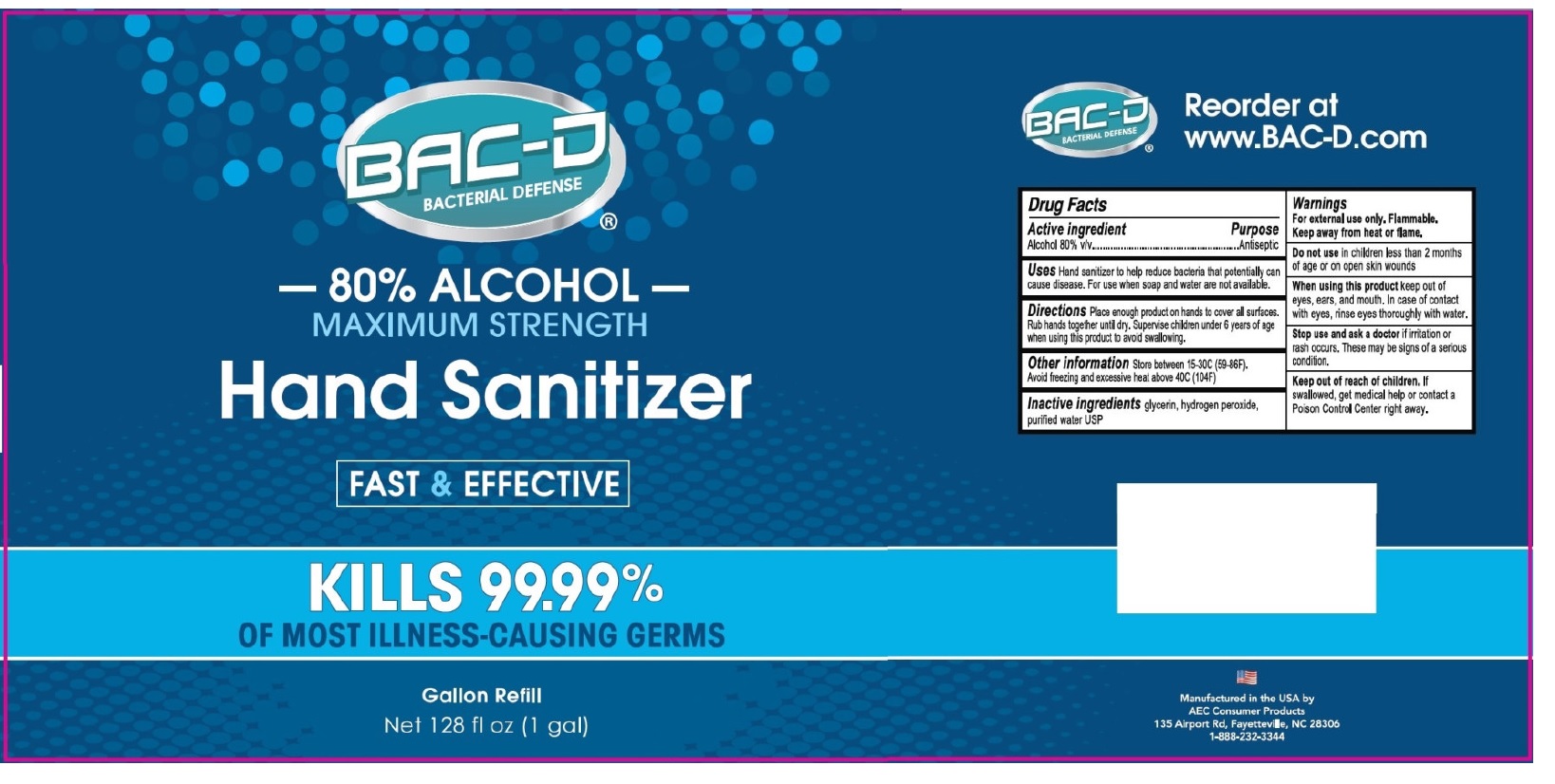 DRUG LABEL: BAC-D Hand Sanitizer
NDC: 86089-950 | Form: LIQUID
Manufacturer: AEC CONSUMER PRODUCTS
Category: otc | Type: HUMAN OTC DRUG LABEL
Date: 20220103

ACTIVE INGREDIENTS: ALCOHOL 80 L/100 L
INACTIVE INGREDIENTS: GLYCERIN; HYDROGEN PEROXIDE; WATER

BAC-D®Hand Sanitizer

Active ingredient

Alcohol 80% v/v

Purpose

Antiseptic

INDICATIONS AND USAGE

Uses Hand sanitizer to help reduce bacteria that potentially can cause disease. For use when soap and water are not available.

DOSAGE AND ADMINISTRATION

Directions Place enough product on hands to cover all surfaces. Rub hands together until dry. Supervise children under 6 years of age when using this product to avoid swallowing.

Other information Store between 15-30ºC (59-86°F). Avoid freezing and excessive heat above 40°C (104°F)

Inactive ingredients glycerin, hydrogen peroxide, purified water USP

Warnings

For external use only. Flammable. Keep away from heat or flame.

Do not use in children less than 2 months of age or on open skin wounds

When using this product keep out of eyes, ears, and mouth. In case of contact with eyes, rinse eyes thoroughly with water.

Stop use and ask a doctor if irritation or rash occurs. These may be signs of a serious condition.

Keep out of reach of children. If swallowed, get medical help or contact a Poison Control Center right away.

MAXIMUM STRENGTH

FAST & EFFECTIVE

KILLS 99.99% OF MOST ILLNESS-CAUSING GERMS

Gallon Refill

Reorder at www.BAC-D.com

Manufactured in the USA by

AEC Consumer Products

135 Airport Rd, Fayetteville, NC 28306

1-888-232-3344